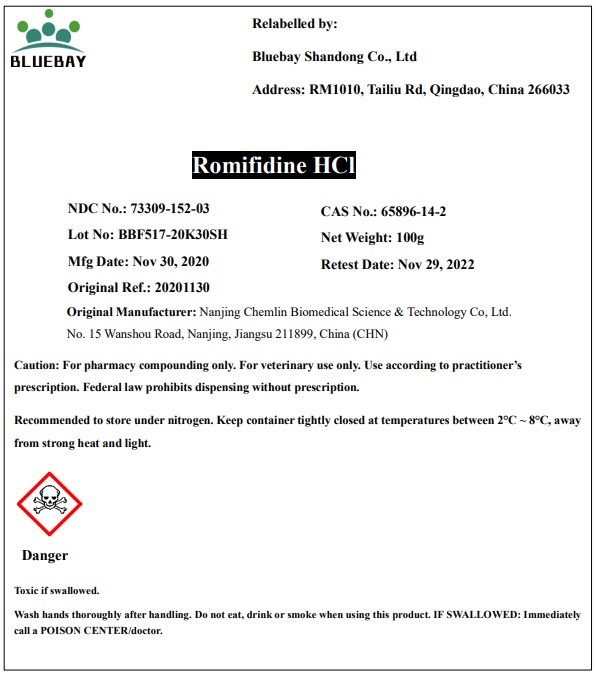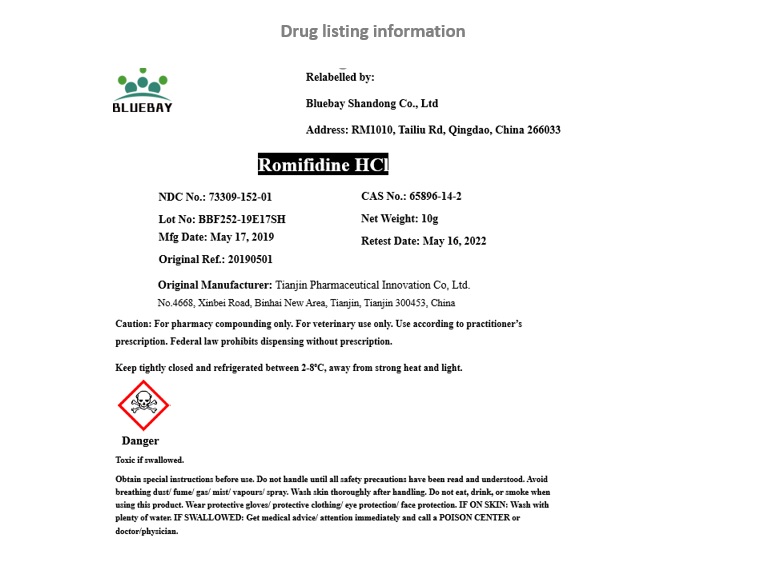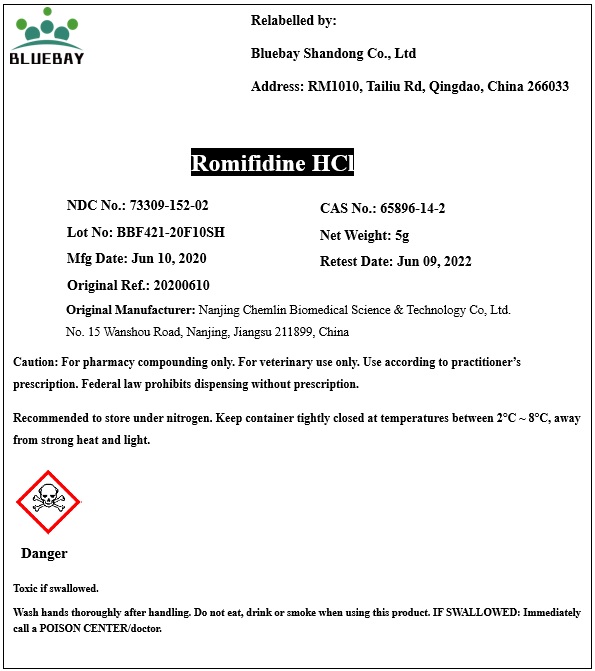 DRUG LABEL: romifidine hcl
NDC: 73309-152 | Form: POWDER
Manufacturer: BLUEBAY SHANDONG CO.,LTD
Category: other | Type: BULK INGREDIENT
Date: 20201202

ACTIVE INGREDIENTS: ROMIFIDINE HYDROCHLORIDE 1 g/1 g

ROMIFIDINE HCL